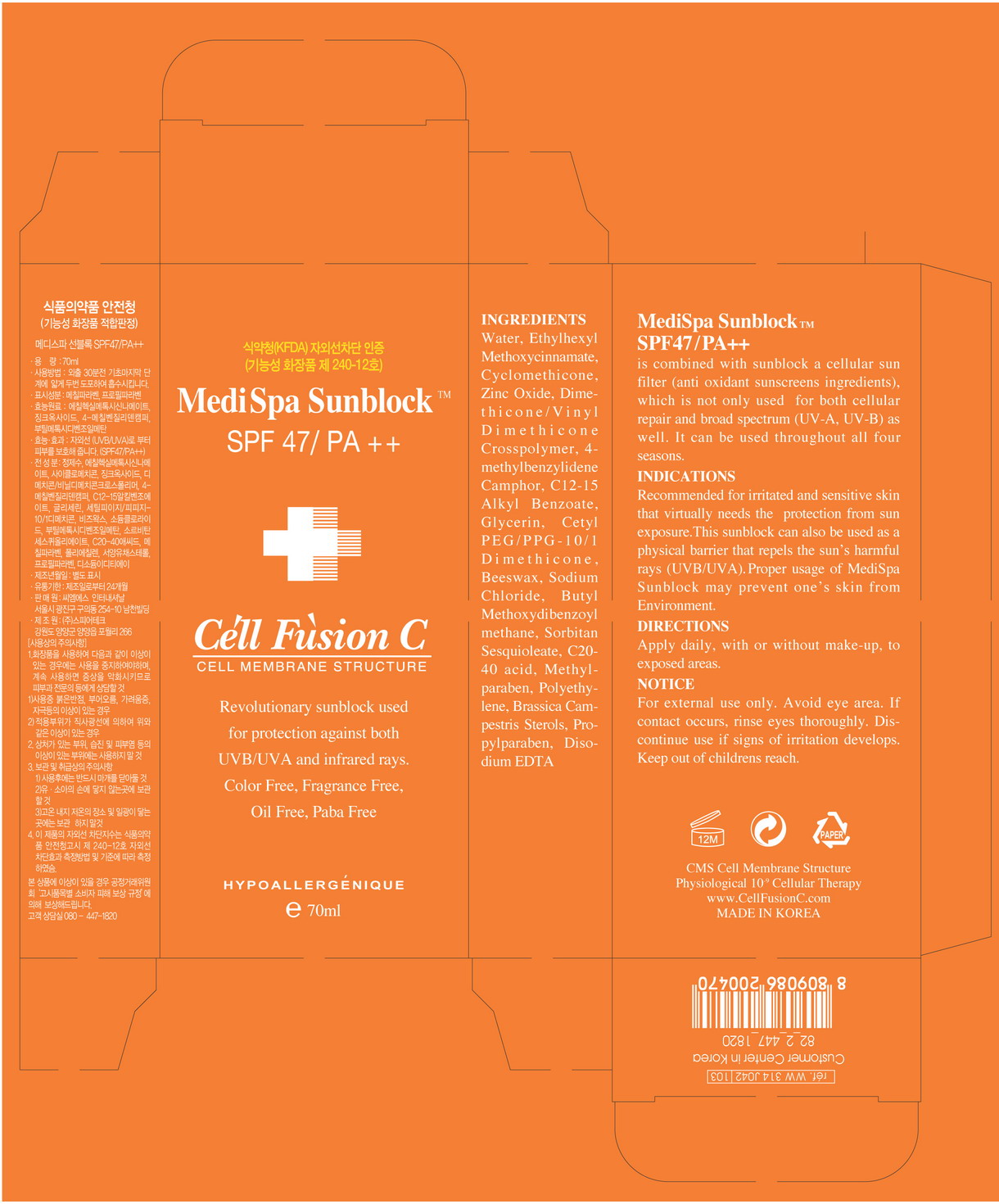 DRUG LABEL: MediSpa Sunblock
NDC: 52554-1001 | Form: CREAM
Manufacturer: Universal Cosmetic Co., Ltd
Category: otc | Type: HUMAN OTC DRUG LABEL
Date: 20100804

ACTIVE INGREDIENTS: ZINC OXIDE 0.05 mL/1 mL; OCTINOXATE 0.07 mL/1 mL; ENZACAMENE 0.03 mL/1 mL; AVOBENZONE 0.005 mL/1 mL

Drug Facts

ACTIVE INGREDIENT

Active Ingredients: Ethylhexyl Methoxycinnamate, Zinc Oxide, 4-Methylbenzylidene camphor, Butyl Mehoxydibenzoylmethane

Uses
■ Perfectly blocks both UVA and UVB rays without stimuli
■ Provides high protection from sunburn
■ Suitable for skin that underwent medical treatment
Warning
For external use only
When using this product
■ Avoid eye area. If contact occurs, rinse eyes thoroughly
■ Discontinue use if signs of irritation develops
Keep out of reach of the children
Direction
■ Rub a proper quantity over the whole face, before finishing skincare.
Other Information
■ store between 20-25 °C (68-77 °F)
■ avoid freezing and excessive heat above 40 °C (104 °F)
■ close cap after use.
Inactive Ingredient
■ Water ■ Cyclomethicone ■ Dimethicone/Vinyl Dimethicone Crosspolymer ■ C12-15 Alkyl Benzoate ■ Glycerin ■ Cetyl PEG/PPG-10/1 Dimethicone ■ Beeswax ■ Sodium Chloride ■ Sorbitan Sesquiolate ■ C20-40 acid ■ Methylparaben ■ Polyethylene ■ Brassica Campestris Sterols ■ Propylparaben ■ Disodium EDTA